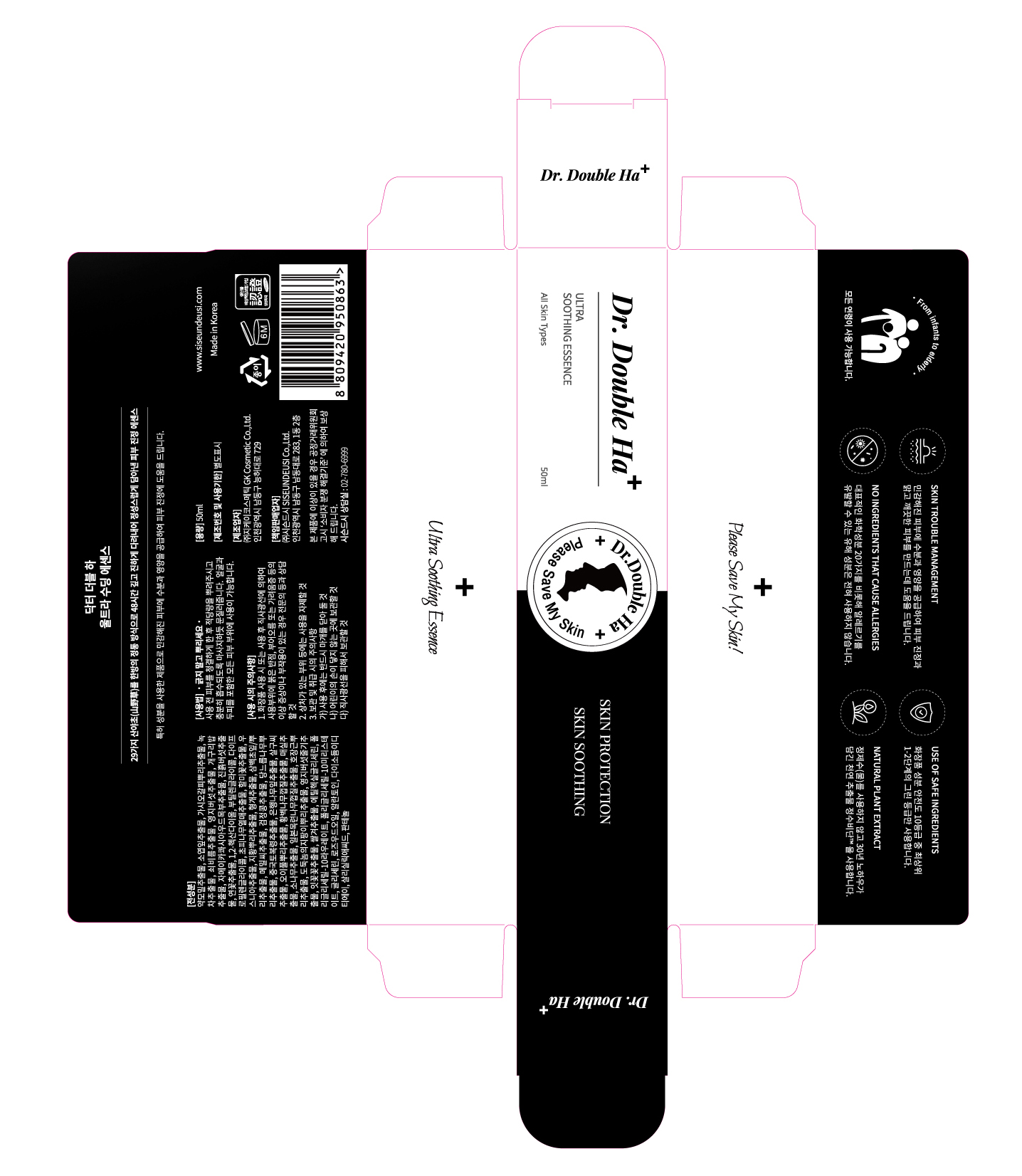 DRUG LABEL: Dr.Double Ha ULTRA SOOTHING ESSENCE
NDC: 70098-0017 | Form: LIQUID
Manufacturer: GK COSMETIC CO., LTD.
Category: otc | Type: HUMAN OTC DRUG LABEL
Date: 20201227

ACTIVE INGREDIENTS: HOUTTUYNIA CORDATA FLOWERING TOP 11.6 g/100 mL; PERILLA FRUTESCENS LEAF 11.6 g/100 mL
INACTIVE INGREDIENTS: BUTYLENE GLYCOL; ALLANTOIN; PANTHENOL

Drug Facts

ACTIVE INGREDIENT

Houttuynia Cordata Extract, Perilla Frutescens Leaf Extract

INACTIVE INGREDIENT

Acanthopanax Senticosus (Eleuthero) Root Extract, Camellia Sinensis Leaf Extract, Portulaca Oleracea Extract, Ganoderma Lucidum (Mushroom) Extract, Spirodela Polyrrhiza Extract, Picrasma Excelsa Wood Extract, Phellinus Linteus Extract, Nelumbium Speciosum Flower Extract, 1,2-Hexanediol, Butylene Glycol, Dipropylene Glycol, Zanthoxylum Piperitum Fruit Extract, Pulsatilla Koreana Extract, Usnea Barbata (Lichen) Extract, Rehmannia Glutinosa Root Extract, Schizonepeta Tenuifolia Extract, Saururus Chinensis Leaf/Root Extract, Polygonum Fagopyrum Seed Extract, Glycine Max (Soybean) Seed Extract, Ulmus Davidiana Root Extract, Poria Cocos Extract, Ginkgo Biloba Leaf Extract, Prunus Armeniaca (Apricot) Kernel Extract, Sanguisorba Officinalis Root Extract, Phellodendron Amurense Bark Extract, Prunus Mume Fruit Extract, Pinus Densiflora Extract, Magnolia Obovata Bark Extract, Polygonum Cuspidatum Root Extract, Sophora Angustifolia Root Extract, Ganoderma Lucidum (Mushroom) Stem Extract, Carthamus Tinctorius (Safflower) Flower Extract, Oryza Sativa (Rice) Bran Extract, Ethylhexylglycerin, Polyglyceryl-10 Laurate, Polyglyceryl-10 Myristate, Glycerin, Aniba Rosodora (Rosewood) Wood Oil, Allantoin, Disodium EDTA, Panthenol

PURPOSE

Skin protectant

keep out of reach of the children

INDICATIONS AND USAGE

Clean the skin before use, spray an appropriate amount, and massage it to absorb enough. It can be used in all skin areas including the face and scalp.

WARNINGS

1. Do not use in the following cases(Eczema and scalp wounds)
2.Side Effects
1)Due to the use of this druf if rash, irritation, itching and symptopms of hypersnesitivity occur dicontinue use and consult your phamacisr or doctor
3.General Precautions
1)If in contact with the eyes, wash out thoroughty with water If the symptoms are servere, seek medical advice immediately
2)This product is for exeternal use only. Do not use for internal use
4.Storage and handling precautions
1)If possible, avoid direct sunlight and store in cool and area of low humidity
2)In order to maintain the quality of the product and avoid misuse
3)Avoid placing the product near fire and store out in reach of children

DOSAGE AND ADMINISTRATION

for external use only